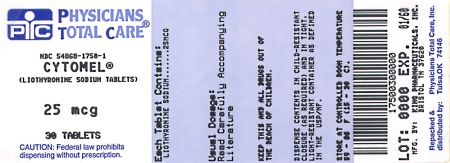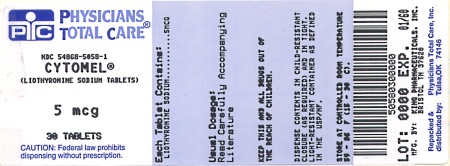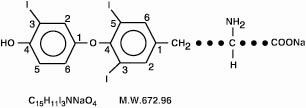 DRUG LABEL: Cytomel
NDC: 54868-5058 | Form: TABLET
Manufacturer: Physicians Total Care, Inc.
Category: prescription | Type: HUMAN PRESCRIPTION DRUG LABEL
Date: 20101230

ACTIVE INGREDIENTS: LIOTHYRONINE SODIUM 5 ug/1 1
INACTIVE INGREDIENTS: CALCIUM SULFATE; GELATIN; STARCH, CORN; STEARIC ACID; SUCROSE; TALC

BOXED WARNING

Drugs with thyroid hormone activity, alone or together with other therapeutic agents, have been used for the treatment of obesity. In euthyroid patients, doses within the range of daily hormonal requirements are ineffective for weight reduction. Larger doses may produce serious or even life-threatening manifestations of toxicity, particularly when given in association with sympathomimetic amines such as those used for their anorectic effects.

DESCRIPTION

Thyroid hormone drugs are natural or synthetic preparations containing tetraiodothyronine (T4, levothyroxine) sodium or triiodothyronine (T3, liothyronine) sodium or both. T4 and T3 are produced in the human thyroid gland by the iodination and coupling of the amino acid tyrosine. T4 contains four iodine atoms and is formed by the coupling of two molecules of diiodotyrosine (DIT). T3 contains three atoms of iodine and is formed by the coupling of one molecule of DIT with one molecule of monoiodotyrosine (MIT). Both hormones are stored in the thyroid colloid as thyroglobulin.

Thyroid hormone preparations belong to two categories: (1) natural hormonal preparations derived from animal thyroid, and (2) synthetic preparations. Natural preparations include desiccated thyroid and thyroglobulin. Desiccated thyroid is derived from domesticated animals that are used for food by man (either beef or hog thyroid), and thyroglobulin is derived from thyroid glands of the hog. The United States Pharmacopeia (USP) has standardized the total iodine content of natural preparations. Thyroid USP contains not less than (NLT) 0.17 percent and not more than (NMT) 0.23 percent iodine, and thyroglobulin contains not less than (NLT) 0.7 percent of organically bound iodine. Iodine content is only an indirect indicator of true hormonal biologic activity.

Cytomel (liothyronine sodium) Tablets contain liothyronine (L-triiodothyronine or LT3), a synthetic form of a natural thyroid hormone, and is available as the sodium salt.

The structural and empirical formulas and molecular weight of liothyronine sodium are given below.

Liothyronine Sodium

L-Tyrosine, O-(4-hydroxy-3-iodophenyl)-3,5-diiodo-, monosodium salt

Twenty-five mcg of liothyronine is equivalent to approximately 1 grain of desiccated thyroid or thyroglobulin and 0.1 mg of L-thyroxine.

Each round, white to off-white Cytomel (liothyronine sodium) tablet contains liothyronine sodium equivalent to liothyronine as follows: 5 mcg debossed KPI and 115; 25 mcg scored and debossed KPI and 116; 50 mcg scored and debossed KPI and 117. Inactive ingredients consist of calcium sulfate, gelatin, starch, stearic acid, sucrose and talc.

CLINICAL PHARMACOLOGY

The mechanisms by which thyroid hormones exert their physiologic action are not well understood. These hormones enhance oxygen consumption by most tissues of the body, increase the basal metabolic rate and the metabolism of carbohydrates, lipids and proteins. Thus, they exert a profound influence on every organ system in the body and are of particular importance in the development of the central nervous system.

Pharmacokinetics

Since liothyronine sodium (T3) is not firmly bound to serum protein, it is readily available to body tissues. The onset of activity of liothyronine sodium is rapid, occurring within a few hours. Maximum pharmacologic response occurs within 2 or 3 days, providing early clinical response. The biological half-life is about 2-1/2 days.

T3 is almost totally absorbed, 95 percent in 4 hours. The hormones contained in the natural preparations are absorbed in a manner similar to the synthetic hormones.

Liothyronine sodium has a rapid cutoff of activity which permits quick dosage adjustment and facilitates control of the effects of overdosage, should they occur.

The higher affinity of levothyroxine (T4) for both thyroid-binding globulin and thyroid-binding prealbumin as compared to triiodothyronine (T3) partially explains the higher serum levels and longer half-life of the former hormone. Both protein-bound hormones exist in reverse equilibrium with minute amounts of free hormone, the latter accounting for the metabolic activity.

INDICATIONS AND USAGE

Thyroid hormone drugs are indicated:

1. As replacement or supplemental therapy in patients with hypothyroidism of any etiology, except transient hypothyroidism during the recovery phase of subacute thyroiditis. This category includes cretinism, myxedema and ordinary hypothyroidism in patients of any age (pediatric patients, adults, the elderly), or state (including pregnancy); primary hypothyroidism resulting from functional deficiency, primary atrophy, partial or total absence of thyroid gland, or the effects of surgery, radiation, or drugs, with or without the presence of goiter; and secondary (pituitary) or tertiary (hypothalamic) hypothyroidism (see WARNINGS).
2. As pituitary thyroid-stimulating hormone (TSH) suppressants, in the treatment or prevention of various types of euthyroid goiters, including thyroid nodules, subacute or chronic lymphocytic thyroiditis (Hashimoto’s) and multinodular goiter.
3. As diagnostic agents in suppression tests to differentiate suspected mild hyperthyroidism or thyroid gland autonomy.

Cytomel (liothyronine sodium) Tablets can be used in patients allergic to desiccated thyroid or thyroid extract derived from pork or beef.

CONTRAINDICATIONS

Thyroid hormone preparations are generally contraindicated in patients with diagnosed but as yet uncorrected adrenal cortical insufficiency, untreated thyrotoxicosis and apparent hypersensitivity to any of their active or extraneous constituents. There is no well-documented evidence from the literature, however, of true allergic or idiosyncratic reactions to thyroid hormone.

WARNINGS

Drugs with thyroid hormone activity, alone or together with other therapeutic agents, have been used for the treatment of obesity. In euthyroid patients, doses within the range of daily hormonal requirements are ineffective for weight reduction. Larger doses may produce serious or even life-threatening manifestations of toxicity, particularly when given in association with sympathomimetic amines such as those used for their anorectic effects.

The use of thyroid hormones in the therapy of obesity, alone or combined with other drugs, is unjustified and has been shown to be ineffective. Neither is their use justified for the treatment of male or female infertility unless this condition is accompanied by hypothyroidism.

Thyroid hormones should be used with great caution in a number of circumstances where the integrity of the cardiovascular system, particularly the coronary arteries, is suspected. These include patients with angina pectoris or the elderly, in whom there is a greater likelihood of occult cardiac disease. In these patients, liothyronine sodium therapy should be initiated with low doses, with due consideration for its relatively rapid onset of action. Starting dosage of Cytomel (liothyronine sodium) Tablets is 5 mcg daily, and should be increased by no more than 5 mcg increments at 2-week intervals. When, in such patients, a euthyroid state can only be reached at the expense of an aggravation of the cardiovascular disease, thyroid hormone dosage should be reduced.

Morphologic hypogonadism and nephrosis should be ruled out before the drug is administered. If hypopituitarism is present, the adrenal deficiency must be corrected prior to starting the drug. Myxedematous patients are very sensitive to thyroid; dosage should be started at a very low level and increased gradually.

Severe and prolonged hypothyroidism can lead to a decreased level of adrenocortical activity commensurate with the lowered metabolic state. When thyroid-replacement therapy is administered, the metabolism increases at a greater rate than adrenocortical activity. This can precipitate adrenocortical insufficiency. Therefore, in severe and prolonged hypothyroidism, supplemental adrenocortical steroids may be necessary. In rare instances the administration of thyroid hormone may precipitate a hyperthyroid state or may aggravate existing hyperthyroidism.

PRECAUTIONS

General

Thyroid hormone therapy in patients with concomitant diabetes mellitus or insipidus or adrenal cortical insufficiency aggravates the intensity of their symptoms. Appropriate adjustments of the various therapeutic measures directed at these concomitant endocrine diseases are required.

The therapy of myxedema coma requires simultaneous administration of glucocorticoids.

Hypothyroidism decreases and hyperthyroidism increases the sensitivity to oral anticoagulants. Prothrombin time should be closely monitored in thyroid-treated patients on oral anticoagulants and dosage of the latter agents adjusted on the basis of frequent prothrombin time determinations. In infants, excessive doses of thyroid hormone preparations may produce craniosynostosis.

Information for Patients

Patients on thyroid hormone preparations and parents of pediatric patients on thyroid therapy should be informed that:

1. Replacement therapy is to be taken essentially for life, with the exception of cases of transient hypothyroidism, usually associated with thyroiditis, and in those patients receiving a therapeutic trial of the drug.
2. They should immediately report during the course of therapy any signs or symptoms of thyroid hormone toxicity, e.g., chest pain, increased pulse rate, palpitations, excessive sweating, heat intolerance, nervousness, or any other unusual event.
3. In case of concomitant diabetes mellitus, the daily dosage of antidiabetic medication may need readjustment as thyroid hormone replacement is achieved. If thyroid medication is stopped, a downward readjustment of the dosage of insulin or oral hypoglycemic agent may be necessary to avoid hypoglycemia. At all times, close monitoring of urinary glucose levels is mandatory in such patients.
4. In case of concomitant oral anticoagulant therapy, the prothrombin time should be measured frequently to determine if the dosage of oral anticoagulants is to be readjusted.
5. Partial loss of hair may be experienced by pediatric patients in the first few months of thyroid therapy, but this is usually a transient phenomenon and later recovery is usually the rule.

Laboratory Tests

Treatment of patients with thyroid hormones requires the periodic assessment of thyroid status by means of appropriate laboratory tests besides the full clinical evaluation. The TSH suppression test can be used to test the effectiveness of any thyroid preparation, bearing in mind the relative insensitivity of the infant pituitary to the negative feedback effect of thyroid hormones. Serum T4 levels can be used to test the effectiveness of all thyroid medications except products containing liothyronine sodium. When the total serum T4 is low but TSH is normal, a test specific to assess unbound (free) T4 levels is warranted. Specific measurements of T4 and T3 by competitive protein binding or radioimmunoassay are not influenced by blood levels of organic or inorganic iodine and have essentially replaced older tests of thyroid hormone measurements, i.e., PBI, BEI and T4 by column.

Drug Interactions Oral Anticoagulants

Thyroid hormones appear to increase catabolism of vitamin K-dependent clotting factors. If oral anticoagulants are also being given, compensatory increases in clotting factor synthesis are impaired. Patients stabilized on oral anticoagulants who are found to require thyroid replacement therapy should be watched very closely when thyroid is started. If a patient is truly hypothyroid, it is likely that a reduction in anticoagulant dosage will be required. No special precautions appear to be necessary when oral anticoagulant therapy is begun in a patient already stabilized on maintenance thyroid replacement therapy.

Insulin or Oral Hypoglycemics

Initiating thyroid replacement therapy may cause increases in insulin or oral hypoglycemic requirements. The effects seen are poorly understood and depend upon a variety of factors such as dose and type of thyroid preparations and endocrine status of the patient. Patients receiving insulin or oral hypoglycemics should be closely watched during initiation of thyroid replacement therapy.

Cholestyramine

Cholestyramine binds both T4 and T3 in the intestine, thus impairing absorption of these thyroid hormones. In vitro studies indicate that the binding is not easily removed. Therefore, 4 to 5 hours should elapse between administration of cholestyramine and thyroid hormones.

Estrogen, Oral Contraceptives

Estrogens tend to increase serum thyroxine-binding globulin (TBg). In a patient with a nonfunctioning thyroid gland who is receiving thyroid replacement therapy, free levothyroxine may be decreased when estrogens are started thus increasing thyroid requirements. However, if the patient’s thyroid gland has sufficient function, the decreased free thyroxine will result in a compensatory increase in thyroxine output by the thyroid. Therefore, patients without a functioning thyroid gland who are on thyroid replacement therapy may need to increase their thyroid dose if estrogens or estrogen-containing oral contraceptives are given.

Tricyclic Antidepressants

Use of thyroid products with imipramine and other tricyclic antidepressants may increase receptor sensitivity and enhance antidepressant activity; transient cardiac arrhythmias have been observed. Thyroid hormone activity may also be enhanced.

Digitalis

Thyroid preparations may potentiate the toxic effects of digitalis. Thyroid hormonal replacement increases metabolic rate, which requires an increase in digitalis dosage.

Ketamine

When administered to patients on a thyroid preparation, this parenteral anesthetic may cause hypertension and tachycardia. Use with caution and be prepared to treat hypertension, if necessary.

Vasopressors

Thyroxine increases the adrenergic effect of catecholamines such as epinephrine and norepinephrine. Therefore, injection of these agents into patients receiving thyroid preparations increases the risk of precipitating coronary insufficiency, especially in patients with coronary artery disease. Careful observation is required.

Drug and Laboratory Test Interactions

The following drugs or moieties are known to interfere with laboratory tests performed in patients on thyroid hormone therapy: androgens, corticosteroids, estrogens, oral contraceptives containing estrogens, iodine-containing preparations and the numerous preparations containing salicylates.

1. Changes in TBg concentration should be taken into consideration in the interpretation of T4 and T3 values. In such cases, the unbound (free) hormone shouldbemeasured. Pregnancy, estrogens and estrogen-containing oral contraceptives increase TBg concentrations. TBg may also be increased during infectious hepatitis. Decreases in TBg concentrations are observed in nephrosis, acromegaly and after androgen or corticosteroid therapy. Familial hyper- or hypo-thyroxine-binding-globulinemias have been described. The incidence of TBg deficiency approximates 1 in 9000. The binding of thyroxine by thyroxine-binding prealbumin (TBPA) is inhibited by salicylates.
2. Medicinal or dietary iodine interferes with all in vivo tests of radioiodine uptake, producing low uptakes which may not be reflective of a true decrease in hormone synthesis.
3. The persistence of clinical and laboratory evidence of hypothyroidism in spite of adequate dosage replacement indicates either poor patient compliance, poor absorption, excessive fecal loss, or inactivity of the preparation. Intracellular resistance to thyroid hormone is quite rare.

Carcinogenesis, Mutagenesis, Impairment of Fertility

A reportedly apparent association between prolonged thyroid therapy and breast cancer has not been confirmed and patients on thyroid for established indications should not discontinue therapy. No confirmatory long-term studies in animals have been performed to evaluate carcinogenic potential, mutagenicity, or impairment of fertility in either males or females.

Pregnancy Category A

Thyroid hormones do not readily cross the placental barrier. The clinical experience to date does not indicate any adverse effect on fetuses when thyroid hormones are administered to pregnant women. On the basis of current knowledge, thyroid replacement therapy to hypothyroid women should not be discontinued during pregnancy.

Nursing Mothers

Minimal amounts of thyroid hormones are excreted in human milk. Thyroid is not associated with serious adverse reactions and does not have a known tumorigenic potential. However, caution should be exercised when thyroid is administered to a nursing woman.

Geriatric Use

Clinical studies of liothyronine sodium did not include sufficient numbers of subjects aged 65 and over to determine whether they respond differently from younger subjects. Other reported clinical experience has not identified differences in responses between the elderly and younger patients. In general, dose selection for an elderly patient should be cautious, usually starting at the low end of the dosing range, reflecting the greater frequency of decreased hepatic, renal, or cardiac function, and of concomitant disease or other drug therapy. This drug is known to be substantially excreted by the kidney, and the risk of toxic reactions to this drug may be greater in patients with impaired renal function. Because elderly patients are more likely to have decreased renal function, care should be taken in dose selection, and it may be useful to monitor renal function.

Pediatric Use

Pregnant mothers provide little or no thyroid hormone to the fetus. The incidence of congenital hypothyroidism is relatively high (1:4000) and the hypothyroid fetus would not derive any benefit from the small amounts of hormone crossing the placental barrier. Routine determinations of serum T4 and/or TSH is strongly advised in neonates in view of the deleterious effects of thyroid deficiency on growth and development.

Treatment should be initiated immediately upon diagnosis and maintained for life, unless transient hypothyroidism is suspected, in which case, therapy may be interrupted for 2 to 8 weeks after the age of 3 years to reassess the condition. Cessation of therapy is justified in patients who have maintained a normal TSH during those 2 to 8 weeks.

ADVERSE REACTIONS

Adverse reactions, other than those indicative of hyperthyroidism because of therapeutic overdosage, either initially or during the maintenance period are rare (see OVERDOSAGE).

In rare instances, allergic skin reactions have been reported with Cytomel (liothyronine sodium) Tablets.

OVERDOSAGE

Signs and Symptoms

Headache, irritability, nervousness, sweating, arrhythmia (including tachycardia), increased bowel motility and menstrual irregularities. Angina pectoris or congestive heart failure may be induced or aggravated. Shock may also develop. Massive overdosage may result in symptoms resembling thyroid storm. Chronic excessive dosage will produce the signs and symptoms of hyperthyroidism.

Treatment Of Overdosage

Dosage should be reduced or therapy temporarily discontinued if signs and symptoms of overdosage appear. Treatment may be reinstituted at a lower dosage. In normal individuals, normal hypothalamic-pituitary-thyroidaxis function is restored in 6 to 8 weeks after thyroid suppression.

Treatment of acute massive thyroid hormone overdosage is aimed at reducing gastrointestinal absorption of the drugs and counteracting central and peripheral effects, mainly those of increased sympathetic activity. Vomiting may be induced initially if further gastrointestinal absorption can reasonably be prevented and barring contraindications such as coma, convulsions, or loss of the gagging reflex. Treatment is symptomatic and supportive. Oxygen may be administered and ventilation maintained. Cardiac glycosides may be indicated if congestive heart failure develops. Measures to control fever, hypoglycemia, or fluid loss should be instituted if needed. Antiadrenergic agents, particularly propranolol, have been used advantageously in the treatment of increased sympathetic activity. Propranolol may be administered intravenously at a dosage of 1 to 3 mg over a 10-minute period or orally, 80 to 160 mg/day, especially when no contraindications exist for its use.

DOSAGE AND ADMINISTRATION

The dosage of thyroid hormones is determined by the indication and must in every case be individualized according to patient response and laboratory findings.

Cytomel (liothyronine sodium) Tablets are intended for oral administration; once-a-day dosage is recommended. Although liothyronine sodium has a rapid cutoff, its metabolic effects persist for a few days following discontinuance.

Mild Hypothyroidism

Recommended starting dosage is 25 mcg daily. Daily dosage then may be increased by up to 25 mcg every 1 or 2 weeks. Usual maintenance dose is 25 to75 mcg daily.

The rapid onset and dissipation of action of liothyronine sodium (T3), as compared with levothyroxine sodium (T4), has led some clinicians to prefer its use in patients who might be more susceptible to the untoward effects of thyroid medication. However, the wide swings in serum T3 levels that follow its administration and the possibility of more pronounced cardiovascular side effects tend to counterbalance the stated advantages.

Cytomel (liothyronine sodium) Tablets may be used in preference to levothyroxine (T4) during radioisotope scanning procedures, since induction of hypothyroidism in those cases is more abrupt and can be of shorter duration. It may also be preferred when impairment of peripheral conversion of T4 to T3 is suspected.

Myxedema

Recommended starting dosage is 5 mcg daily. This may be increased by 5 to 10 mcg daily every 1 or 2 weeks. When 25 mcg daily is reached, dosage may be increased by 5 to 25 mcg every 1 or 2 weeks until a satisfactory therapeutic response is attained. Usual maintenance dose is 50 to 100 mcg daily.

Myxedema Coma

Myxedema coma is usually precipitated in the hypothyroid patient of long standing by intercurrent illness or drugs such as sedatives and anesthetics and should be considered a medical emergency.

An intravenous preparation of liothyronine sodium is marketed by Jones Pharma Incorporated, under the trade name Triostat® for use in myxedema coma/precoma.

Congenital Hypothyroidism

Recommended starting dosage is 5 mcg daily, with a 5 mcg increment every 3 to 4 days until the desired response is achieved. Infants a few months old may require only 20 mcg daily for maintenance. At 1 year, 50 mcg daily may be required. Above 3 years, full adult dosage may be necessary (see PRECAUTIONS, Pediatric Use).

Simple (non-toxic) Goiter

Recommended starting dosage is 5 mcg daily. This dosage may be increased by 5 to 10 mcg daily every 1 or 2 weeks. When 25 mcg daily is reached, dosage may be increased every week or two by 12.5 or 25 mcg. Usual maintenance dosage is 75 mcg daily.

In the elderly or in pediatric patients, therapy should be started with 5 mcg daily and increased only by 5 mcg increments at the recommended intervals.

When switching a patient to Cytomel (liothyronine sodium) Tablets from thyroid, L-thyroxine or thyroglobulin, discontinue the other medication, initiate Cytomel at a low dosage, and increase gradually according to the patient's response. When selecting a starting dosage, bear in mind that this drug has a rapid onset of action, and that residual effects of the other thyroid preparation may persist for the first several weeks of therapy.

Thyroid Supression Therapy

Administration of thyroid hormone in doses higher than those produced physiologically by the gland results in suppression of the production of endogenous hormone. This is the basis for the thyroid suppression test and is used as an aid in the diagnosis of patients with signs of mild hyperthyroidism in whom baseline laboratory tests appear normal or to demonstrate thyroid gland autonomy in patients with Graves’ ophthalmopathy. ^131I uptake is determined before and after the administration of the exogenous hormone. A 50% or greater suppression of uptake indicates a normal thyroid-pituitary axis and thus rules out thyroid gland autonomy.

Cytomel (liothyronine sodium) Tablets are given in doses of 75 to 100 mcg/day for 7 days, and radioactive iodine uptake is determined before and after administration of the hormone. If thyroid function is under normal control, the radioiodine uptake will drop significantly after treatment. Cytomel (liothyronine sodium) Tablets should be administered cautiously to patients in whom there is a strong suspicion of thyroid gland autonomy, in view of the fact that the exogenous hormone effects will be additive to the endogenous source.

HOW SUPPLIED

Cytomel (liothyronine sodium) Tablets:

5 mcg

Bottles of 10 | NDC 54868-5058-3
Bottles of 30 | NDC 54868-5058-1
Bottles of 60 | NDC 54868-5058-2
Bottles of 100 | NDC 54868-5058-0

25 mcg

Bottles of 10 | NDC 54868-1750-2
Bottles of 30 | NDC 54868-1750-1
Bottles of 100 | NDC 54868-1750-0

Store between 15° and 30°C (59° and 86°F).

Prescribing Information as of March 2004.

Manufactured by: King Pharmaceuticals, Inc., Bristol, TN 37620

Relabeling and Repackaging by:
Physicians Total Care, Inc.
Tulsa, OK 74146

PRINCIPAL DISPLAY PANEL

Cytomel (liothyronine sodium) Tablets

5 mcg

25 mcg